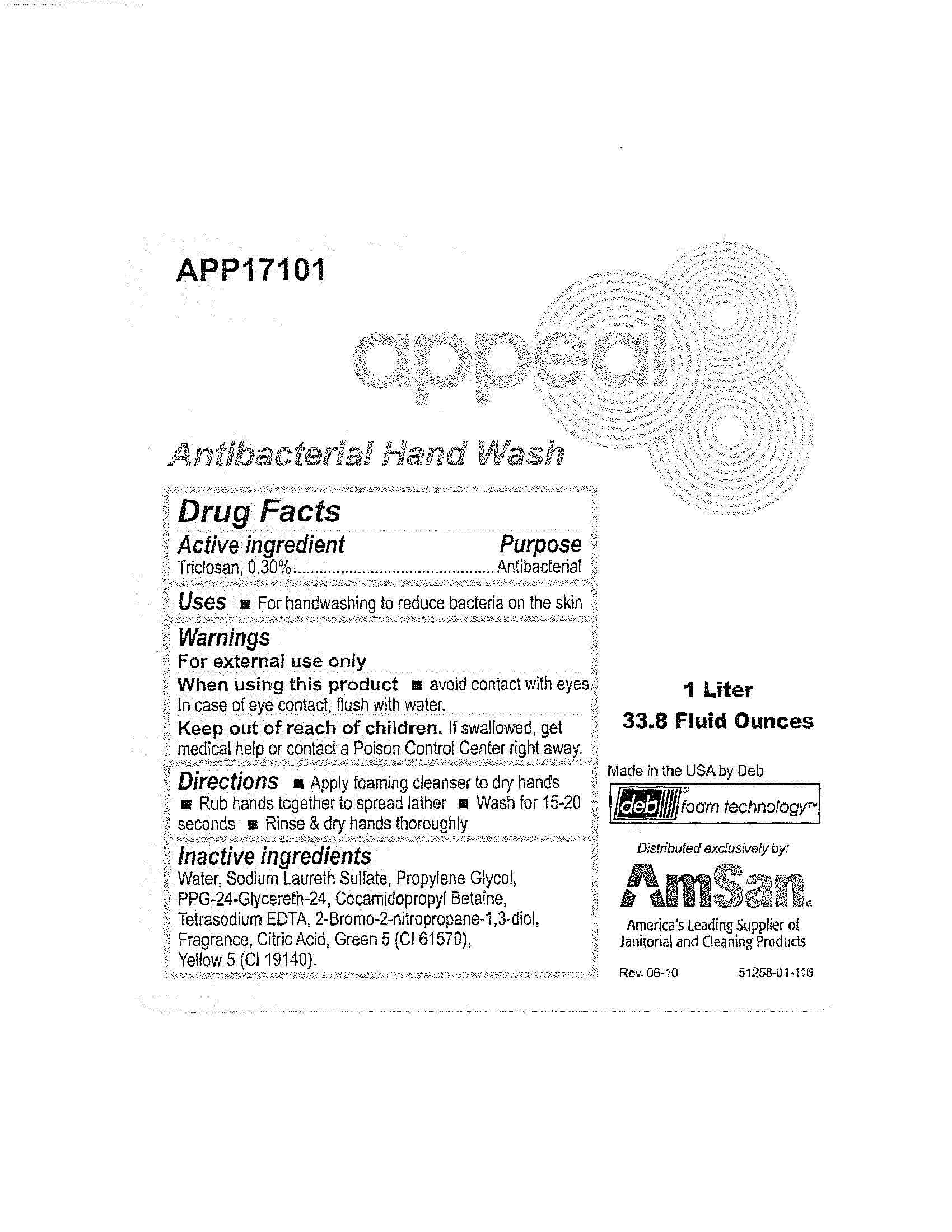 DRUG LABEL: Appeal Antibacterial Hand Wash
NDC: 11084-105 | Form: LIQUID
Manufacturer: Deb USA, Inc.
Category: otc | Type: HUMAN OTC DRUG LABEL
Date: 20100928

ACTIVE INGREDIENTS: TRICLOSAN 0.30 mL/100 mL
INACTIVE INGREDIENTS: WATER; SODIUM LAURETH SULFATE; PROPYLENE GLYCOL; COCAMIDOPROPYL BETAINE; EDETATE SODIUM; ANHYDROUS CITRIC ACID; D&C GREEN NO. 5; FD&C YELLOW NO. 5

Drug Facts

Active ingredient

Triclosan, 0.30%

Purpose

Antibacterial

Uses

For handwashing to reduce bacteria on skin

Warnings

For external use only

When using this product avoid contact with eyes.

In case of eye contact, flush with water.

Keep out of reach of children.

If swallowed, get medical help or contact a Poison Control Center right away.

Directions

Apply foaming cleanser to dry hands

Rub hands together to spread lather

Wash for 15-20 seconds

Rinse and dry hands thoroughly

Inactive ingredients

Water, Sodium Laureth Sulfate, Propylene Glycol, PPG-24-Glycereth-24, Cocamidopropyl Betaine, Tetrasodium EDTA, 2-Bromo-2-nitropropane-1,3-diol, Fragrance, Citric Acid, Green 5 (CI 61570), Yellow 5 (CI 19140).

PACKAGE LABEL

APP17101

appeal

Antibacterial Hand Wash

1 Liter

33.8 Fluid Ounces

Made in the USA by Deb

deb foam technology

Distributed exclusively by:

AmSan

America's Leading Supplier of Janitorial and Cleaning Products